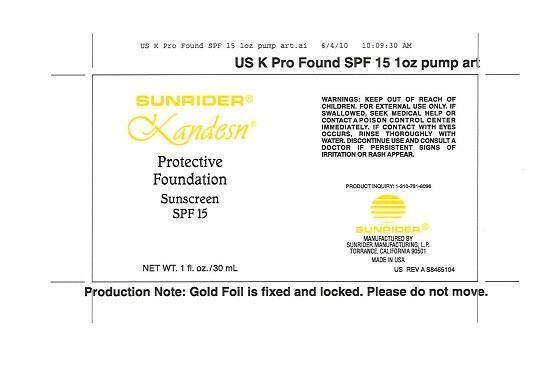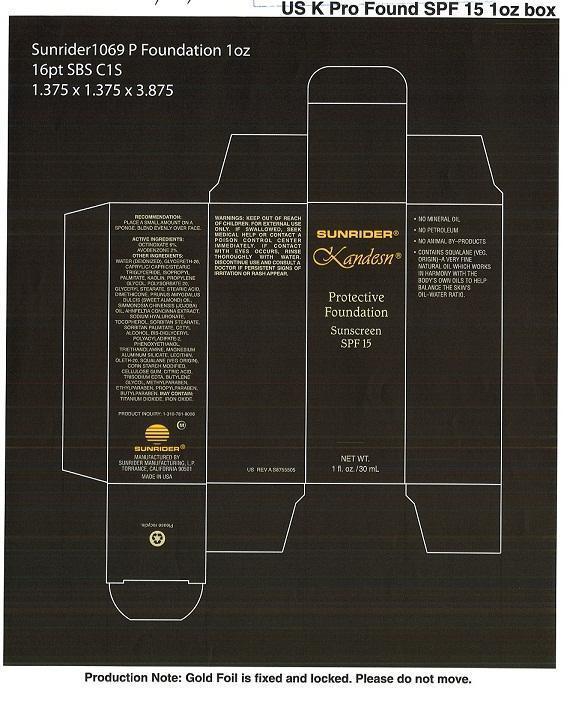 DRUG LABEL: Protective Foundation Sunscreen SPF 15
NDC: 62191-007 | Form: EMULSION
Manufacturer: Sunrider Manufacturing L.P.
Category: otc | Type: HUMAN OTC DRUG LABEL
Date: 20130213

ACTIVE INGREDIENTS: AVOBENZONE 0.02 g/1 g; OCTINOXATE 0.06 g/1 g
INACTIVE INGREDIENTS: 1-BUTENE; AHNFELTIOPSIS CONCINNA; ALMOND OIL; BUTYLPARABEN; CARBOXYMETHYLCELLULOSE SODIUM; CETYL ALCOHOL; CITRIC ACID MONOHYDRATE; DIMETHICONE; EDETATE TRISODIUM; GLYCERETH-26; GLYCERYL MONOSTEARATE; HYALURONATE SODIUM; ISOPROPYL PALMITATE; KAOLIN; MAGNESIUM ALUMINUM SILICATE; OLETH-20; PHENOXYETHANOL; POLYSORBATE 20; PROPYLENE GLYCOL; SORBITAN MONOPALMITATE; SORBITAN MONOSTEARATE; SQUALENE; STEARIC ACID; TOCOPHEROL; TRICAPRIN; TRICAPRYLIN; TROLAMINE; WATER

Protective Foundation Sunscreen SPF 15

PURPOSE

USES: HELPS PREVENT SUNBURNS.

DOSAGE AND ADMINISTRATION

RECOMMENDATION: PLACE A SMALL AMOUNT ON A SPONGE, BLEND EVENLY OVER FACE

ACTIVE INGREDIENTS:

OCTINOXATE 6%
AVOBENZONE 2%

INACTIVE INGREDIENT

OTHER INGREDIENTS: WATER (DEIONIZED), GLYCERETH-26, CAPRYLIC/CAPRIC/STEARIC TRIGLLYCERIDE, ISOPROPYL PALMITATE, KAOLIN, PROPYLENE GLYCOL, POLYSORBATE 20, GLYCERYL STEARATE, STEARIC ACID, DIMETHICONE, PRUNUS AMYGDALUS DULCIS (SWEEK ALMOND)OIL, SIMMONDSIA CHINENSIS (JOJOBA) OIL, AHNFELTIA CONCINNA EXTRACT, SODIUM HYALURONATE, TOCOPHEROL, SORBITAN STEARATE, SORBITAN PALMITATE, CETYL ALCOHOL, BIS-DIGLYCERYL POLYACYLADIPATE-2, PHENOXYETHANOL, TRIETHANOLAMINE, MAGNESIUM ALUMINUM SILICATE, LECITHIN, OLETH-20, SQUALENE (VEG ORIGIN), CORN STARCH MODIFIED, CELLULOSE GUM, CITRIC ACID, TRISODIUM EDTA, BUTYLENE, BUTYLPARABEN, MAY CONTAIN:TITANIUM DIOXIDE, IRON OXIDE.

WARNINGS

WARNINGS: FOR EXTERNAL USE ONLY, IF SWALLOWED SEEK MEDICAL HELP OR CONTACT A POISON CONTROL CENTER IMMEDIATELY, IF CONTACT WITH EYES OCCURS, RINSE THOROUGHLY WITH WATER, DISCONTINUE USE AND CONSULT A DOCTOR IF PERSISTENT SIGNS OF IRRITATION OR RASH APPEAR.

KEEP OUT OF REACH OF CHILDREN

PACKAGE LABEL

cartonpump